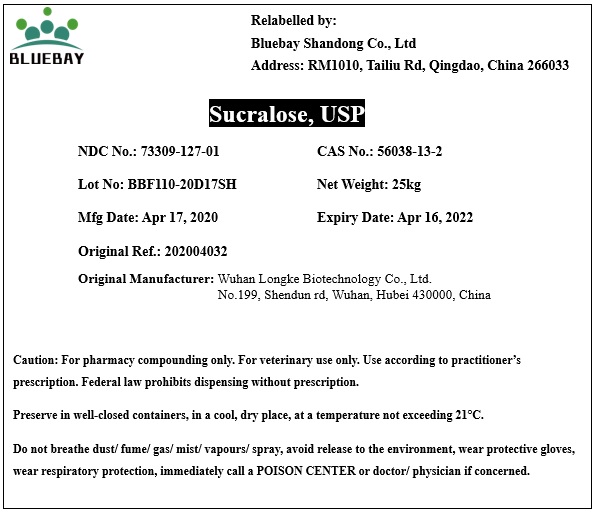 DRUG LABEL: Sucralose
NDC: 73309-127 | Form: POWDER
Manufacturer: BLUEBAY SHANDONG CO.,LTD
Category: other | Type: BULK INGREDIENT
Date: 20200422

ACTIVE INGREDIENTS: SUCRALOSE 1 kg/1 kg

Sucralose